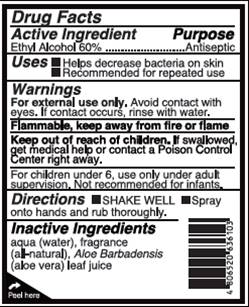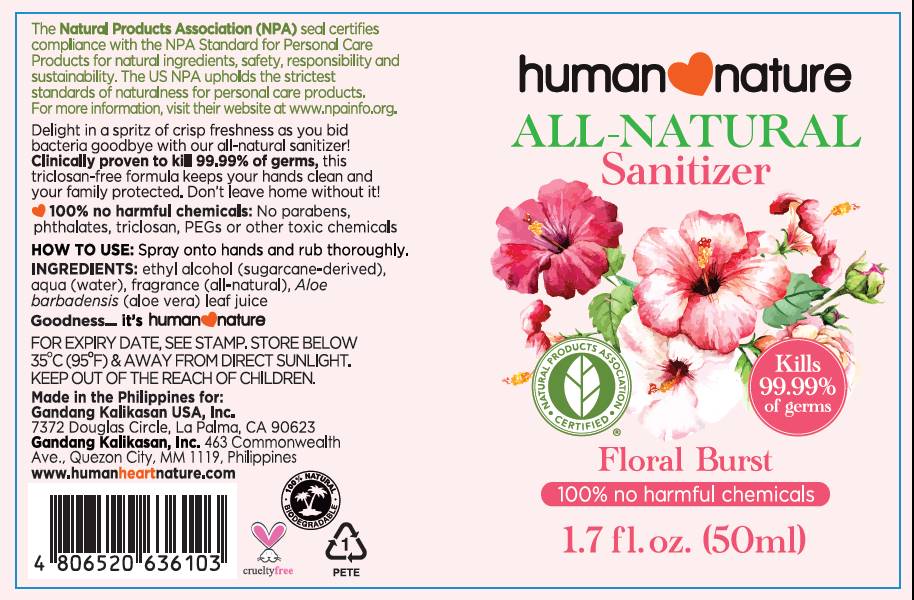 DRUG LABEL: Sanitizer
NDC: 70143-1000 | Form: SPRAY
Manufacturer: Gandang Kalikasan USA Inc.
Category: otc | Type: HUMAN OTC DRUG LABEL
Date: 20191230

ACTIVE INGREDIENTS: ALCOHOL 60 mL/100 mL
INACTIVE INGREDIENTS: WATER; ALOE VERA LEAF

All-Natural Sanitizer Floral Burst

Active Ingredient

Ethyl alcohol 60%

Uses:

- Helps decrease bacteria on skin
- Recommended for repeated use

Purpose

Antiseptic

Warnings

For external use only. Avoid contact with eyes. If contact occurs, rinse with water.

Flammable, keep away from fire or flame.

Keep out of reach of children. If swallowed, get medical help or contat a Poison Control Center right away.

For children under 6, use only under adult supervision. Not recommended for infants.

Directions

Shake well.

DOSAGE AND ADMINISTRATION

Spray onto hands and rub thorughly.

Inactive Ingredients

aqua (water), fragrance (all-natural), Aloe barbadensis (aloe vera) leaf juice